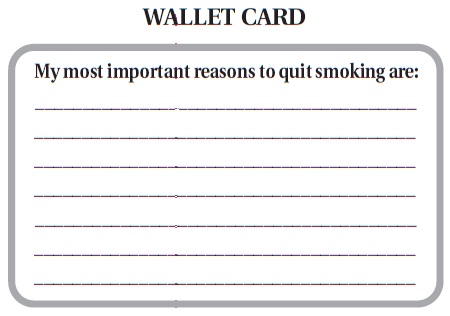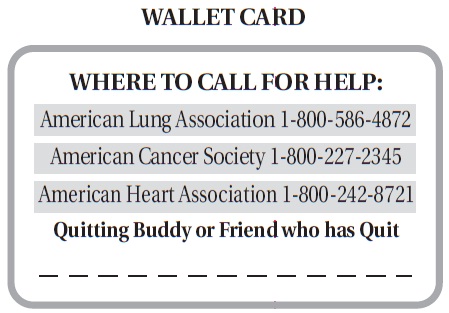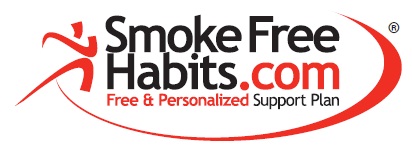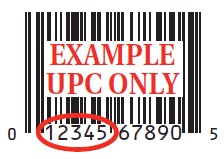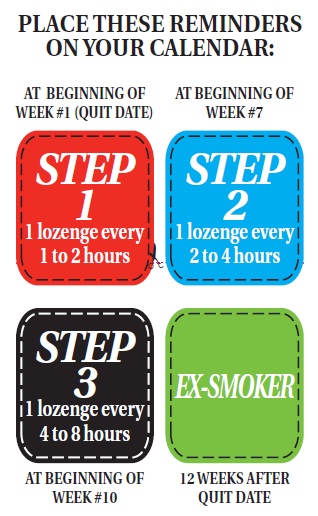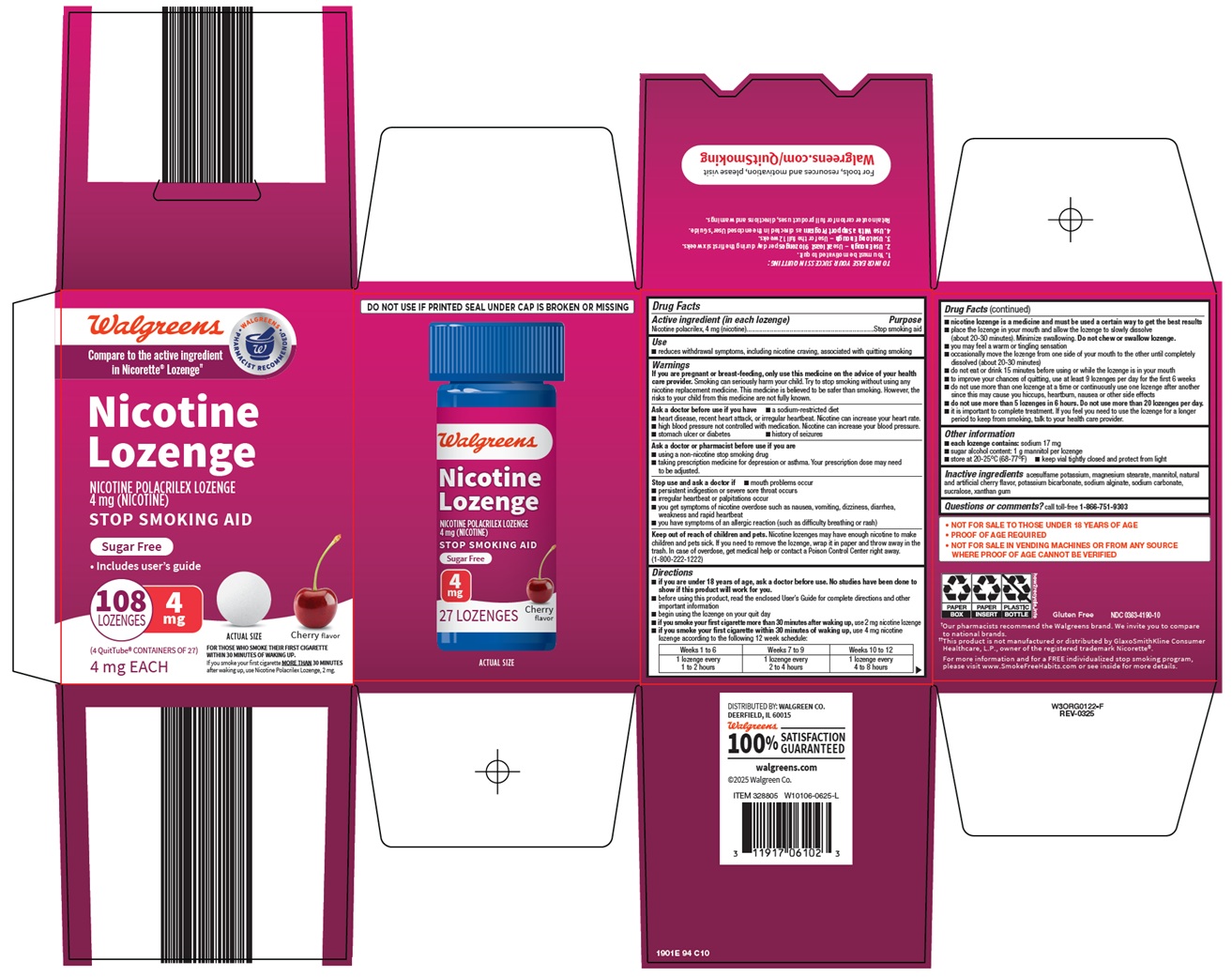 DRUG LABEL: Nicotine
NDC: 0363-4190 | Form: LOZENGE
Manufacturer: Walgreen Company
Category: otc | Type: HUMAN OTC DRUG LABEL
Date: 20260301

ACTIVE INGREDIENTS: NICOTINE 4 mg/1 1
INACTIVE INGREDIENTS: POLACRILIN; ACESULFAME POTASSIUM; MAGNESIUM STEARATE; MANNITOL; POTASSIUM BICARBONATE; SODIUM ALGINATE; SODIUM CARBONATE; SUCRALOSE; XANTHAN GUM

Walgreen Co. Nicotine Lozenge Drug Facts

Active ingredient (in each lozenge)

Nicotine polacrilex, 4 mg (nicotine)

Purpose

Stop smoking aid

Use

- reduces withdrawal symptoms, including nicotine craving, associated with quitting smoking

Warnings

If you are pregnant or breast-feeding,

only use this medicine on the advice of your health care provider. Smoking can seriously harm your child. Try to stop smoking without using any nicotine replacement medicine. This medicine is believed to be safer than smoking. However, the risks to your child from this medicine are not fully known.

Ask a doctor before use if you have

- a sodium-restricted diet
- heart disease, recent heart attack, or irregular heartbeat. Nicotine can increase your heart rate.
- high blood pressure not controlled with medication. Nicotine can increase your blood pressure.
- stomach ulcer or diabetes
- history of seizures

Ask a doctor or pharmacist before use if you are

- using a non-nicotine stop smoking drug
- taking prescription medicine for depression or asthma. Your prescription dose may need to be adjusted.

Stop use and ask a doctor if

- mouth problems occur
- persistent indigestion or severe sore throat occurs
- irregular heartbeat or palpitations occur
- you get symptoms of nicotine overdose such as nausea, vomiting, dizziness, diarrhea, weakness and rapid heartbeat
- you have symptoms of an allergic reaction (such as difficulty breathing or rash)

Keep out of reach of children and pets.

Nicotine lozenges may have enough nicotine to make children and pets sick. If you need to remove the lozenge, wrap it in paper and throw away in the trash. In case of overdose, get medical help or contact a Poison Control Center right away. (1-800-222-1222)

Directions

- if you are under 18 years of age, ask a doctor before use. No studies have been done to show if this product will work for you.
- before using this product, read the enclosed User’s Guide for complete directions and other important information
- begin using the lozenge on your quit day
- if you smoke your first cigarette more than 30 minutes after waking up, use 2 mg nicotine lozenge
- if you smoke your first cigarette within 30 minutes of waking up, use 4 mg nicotine lozenge according to the following 12 week schedule:

Weeks 1 to 6 | Weeks 7 to 9 | Weeks 10 to 12
1 lozenge every; 1 to 2 hours | 1 lozenge every; 2 to 4 hours | 1 lozenge every; 4 to 8 hours

- nicotine lozenge is a medicine and must be used a certain way to get the best results
- place the lozenge in your mouth and allow the lozenge to slowly dissolve (about 20-30 minutes). Minimize swallowing. Do not chew or swallow lozenge.
- you may feel a warm or tingling sensation
- occasionally move the lozenge from one side of your mouth to the other until completely dissolved (about 20-30 minutes)
- do not eat or drink 15 minutes before using or while the lozenge is in your mouth
- to improve your chances of quitting, use at least 9 lozenges per day for the first 6 weeks
- do not use more than one lozenge at a time or continuously use one lozenge after another since this may cause you hiccups, heartburn, nausea or other side effects
- do not use more than 5 lozenges in 6 hours. Do not use more than 20 lozenges per day.
- it is important to complete treatment. If you feel you need to use the lozenge for a longer period to keep from smoking, talk to your health care provider.

Other information

- each lozenge contains: sodium 17 mg
- sugar alcohol content: 1 g mannitol per lozenge
- store at 20-25°C (68-77°F)
- keep vial tightly closed and protect from light

Inactive ingredients

acesulfame potassium, magnesium stearate, mannitol, natural and artificial cherry flavor, potassium bicarbonate, sodium alginate, sodium carbonate, sucralose, xanthan gum

Questions or comments?

call toll-free 1-866-751-9303

Consumer Information

Nicotine Polacrilex Lozenge

2 mg and 4 mg User's Guide

How to Use Nicotine Polacrilex Lozenges and Tips to Help You Quit Smoking.

- Not for sale to those under 18 years of age
- Proof of age required
- Not for sale in vending machines or from any source where proof of age cannot be verified

PLANNING YOUR SUCCESS

1) The key to accomplishing anything important is commitment. When it comes to quitting smoking, that is especially true. Nicotine Polacrilex Lozenges can help if you really want to quit. Nicotine Polacrilex Lozenges help reduce withdrawal symptoms including nicotine craving associated with quitting smoking.
2) Your chances of staying off cigarettes are much better if you start with at least 9 Nicotine Polacrilex Lozenges daily. For best results, use the lozenges on a regular schedule (as outlined in this User's Guide).
3) Start using Nicotine Polacrilex Lozenges on your quit date.
4) This User's Guide outlines a 12-week plan for Nicotine Polacrilex Lozenges. Even though you may feel confident about your non-smoking status after a few weeks, it's important to stick with the plan to help you remain smoke free. Even a single cigarette can put you right back to square one.
5) Nicotine Polacrilex Lozenges work best when used together with a support plan. See information to the right for instructions on enrollment in the SmokeFreeHabits.com Free & Personalized Support Plan.
6) After the first six weeks, start using fewer Nicotine Polacrilex Lozenges, as directed in the instructions, gradually reducing your use over the next six weeks. If you feel the need to use the lozenges for a longer period to keep from smoking, talk to your health care provider.
7) If you have questions about using Nicotine Polacrilex Lozenges, please talk to your pharmacist, family doctor, or call toll-free 1-866-751-9303.

YES! YOU WANT TO QUIT.

Wonderful. You've made the most important decision of all, to stop smoking. And by choosing Nicotine Polacrilex Lozenges to help you, you're starting on the right path. Now remember, using Nicotine Polacrilex Lozenges doesn't just mean taking a Nicotine Polacrilex Lozenge. It means setting and following a program like the one we suggest in this User's Guide.

Your own success depends on your effort, your level of addiction to tobacco, and your commitment to following your program.

LET'S FACE IT.

Quitting smoking isn't easy! You or someone you know may have tried unsuccessfully. That's okay. It's hard to stop smoking the first time you try. The important part is to learn from your previous attempts, consider what went wrong and keep trying to quit until you succeed. Look to this User's Guide for support as you undergo this terrific task. The guide includes important information on how to use Nicotine Polacrilex Lozenges and also gives you tips to help you stop smoking. Refer back to it often for advice, answers, and encouragement to help you stay on track.

GET MOTIVATED. STAY MOTIVATED.

Everyone has a reason for quitting–whether you're concerned about your health, your appearance, family or peer pressure, or the effect of secondhand smoke on your loved ones–all of the above, or something else entirely. Whatever your reasons, write them down. There's a wallet card on the bottom of this User's Guide. Write your reasons on the card and carry it with you. When you have an urge to smoke or experience a difficult moment it can help you focus on your reasons for quitting. Lots of people quit with a co-worker, spouse or friend and use them as a quitting buddy. You can help each other out by providing extra encouragement in tough moments.

There may be support groups in your area for people trying to quit. Call your local chapter of the American Lung Association, American Cancer Society or American Heart Association for further information. Toll free phone numbers are printed on the wallet card on the bottom of this User's Guide.

UNDERSTANDING THE DOUBLE-EDGED SWORD.

Smoking has two addictive components, a physical and a mental need for the nicotine in tobacco. You need to conquer both to succeed. Nicotine Polacrilex Lozenges can ease your physical nicotine addiction. But your readiness and resolve are necessary to help overcome the mental side of your cigarette dependence. So once you're ready, it's time to begin. But first, read and consider the following important warnings.

IMPORTANT WARNINGS

This product is only for those who want to stop smoking.

If you are pregnant or breast-feeding, only use this medicine on the advice of your health care provider. Smoking can seriously harm your child. Try to stop smoking without using any nicotine replacement medicine. This medicine is believed to be safer than smoking. However, the risks to your child from this medicine are not fully known.

Ask a doctor before use if you have

- a sodium-restricted diet
- heart disease, recent heart attack or irregular heartbeat. Nicotine can increase your heart rate.
- high blood pressure not controlled with medication. Nicotine can increase your blood pressure.
- stomach ulcers or diabetes.
- history of seizures

Ask a doctor or pharmacist before use if you are

- using a non-nicotine stop smoking drug
- taking prescription medicine for depression or asthma. Your prescription dose may need to be adjusted.

Stop use and ask a doctor if

- mouth problems occur
- persistent indigestion or severe sore throat occurs
- irregular heartbeat or palpitations occur
- you get symptoms of nicotine overdose such as nausea, vomiting, dizziness, diarrhea, weakness or rapid heartbeat
- you have symptoms of an allergic reaction (such as difficulty breathing or rash)

Keep out of reach of children and pets. Nicotine lozenges may have enough nicotine to make children and pets sick. If you need to remove the lozenge, wrap it in paper and throw away in the trash. In case of overdose, get medical help or contact a Poison Control Center right away. (1-800-222-1222)

YOU'RE READY TO START.

Okay, you're ready. To become a non-smoker, start today. Now before you do anything else, you have a bit of planning to do. Read this User's Guide all the way through. You want to make sure you bought the right dose to start. If you typically smoke your first cigarette within 30 minutes of waking up, use the 4 mg Nicotine Polacrilex Lozenges. If you smoke your first cigarette more than 30 minutes after waking up, use the 2 mg Nicotine Polacrilex Lozenges.

Next, plan your quitting schedule. Get a calendar to follow your progress and mark the following four important dates (see the reminders on the left side of this leaflet).

THE PROGRAM

STEP 1. (Weeks 1-6) Starting on your quit date it's best to use at least 9 Nicotine Polacrilex Lozenges each day, one every 1-2 hours.

First choose the day you plan to quit (make it soon). Place the Step 1 reminder on this date. That's the day you will start using Nicotine Polacrilex Lozenges to calm your cravings for nicotine and help you stay smoke free. Prior to the quit date, get rid of all your cigarettes to remove temptations and make it more difficult to start smoking again.

Use a Nicotine Polacrilex Lozenge every 1 to 2 hours and at least 9 lozenges each day for the first 6 weeks to help prevent unexpected cravings and improve your chances of quitting. These aren't ordinary lozenges. Place the lozenge in your mouth and allow the lozenge to slowly dissolve (about 20-30 minutes). Minimize swallowing. Do not chew or swallow the lozenge. You may feel a warm or tingling sensation. Occasionally move the lozenge from one side of your mouth to the other until completely dissolved (about 20 to 30 minutes). Remember to read the USING Nicotine Polacrilex LOZENGES PROPERLY section before you take your first Nicotine Polacrilex Lozenge.

STEP 2. (The next three weeks, that is weeks 7-9). At the beginning of week 7 start using fewer Nicotine Polacrilex Lozenges, one every 2-4 hours.

After six weeks, you should wait a little longer between lozenges, one lozenge every two to four hours. This will help you gradually use fewer Nicotine Polacrilex Lozenges. Put the Step 2 reminder on the first day of week 7 to help remind you when to start reducing the number of Nicotine Polacrilex Lozenges you take.

STEP 3. (The last three weeks, that is weeks 10-12). At the beginning of week 10, reduce Nicotine Polacrilex Lozenge use even further, one every 4-8 hours.

At the beginning of week 10 further decrease the number of Nicotine Polacrilex Lozenges you use each day to reduce the amount of nicotine you get. You should do this by using one lozenge every 4 to 8 hours. Put the Step 3 reminder on the first day of week 10 so you know when you should be starting this last step to becoming smoke and nicotine-free.

END. At the end of week 12 you’ll complete Nicotine Polacrilex Lozenges therapy.

Put the “EX-SMOKER” reminder on your calendar on the date 12 weeks after the day you stopped smoking and started using Nicotine Polacrilex Lozenges.

BE PREPARED.

Since smoking is an addiction, it is hard to quit. Even after you stop, there will be times when you WANT a cigarette, sometimes strongly. (See also section on "Challenges To Watch For"). The best defense is to be prepared. Plan now for handling tough times so you don't give in. For example: think about situations when you usually get a craving for cigarettes or where you think you might experience strong cravings. Try to avoid these situations where you can (for example, avoid spending time with smokers, or drinking alcohol, if those things tempt you to smoke).

Change your habits. For example, take your coffee break somewhere else. Take a walk. In other words, break the association between your usual habits and cigarettes.

If you do encounter a situation where you feel a strong craving, fight it! Take a break from the situation; keep yourself busy or distracted with other activities. Remind yourself why you want to quit, and above all, remind yourself that having "just one" really will hurt your goal of quitting!

To prepare for tough situations, assemble a "survival package" – items that can keep you distracted in case you get a craving. For example, you may include cinnamon gum or hard candy, relaxing music, and things to keep your hands busy like a smooth stone, paper clips, or a rubber ball.

Track your progress as you quit. Keep a journal. Write down how many pieces of Nicotine Polacrilex Lozenges you use each day. Note if and when you get a craving. If you slip and have a cigarette, don't give up. Stop smoking again and get back on your program with Nicotine Polacrilex Lozenges.

Establish your support network. Keep friends' and family members' phone numbers ready to get the moral support you need. Before quitting, ask friends and family to support and encourage you. Think of specific ways they can help.

Reward yourself. Set aside little gifts to yourself such as a CD or video, which you can earn by overcoming difficult hurdles.

HOW Nicotine Polacrilex LOZENGES WORK.

Nicotine Polacrilex Lozenges are a form of Nicotine Replacement Therapy. They deliver nicotine to your body, temporarily relieving craving and nicotine withdrawal symptoms when you quit smoking. But unlike cigarettes, Nicotine Polacrilex Lozenges deliver a lower, steady level of nicotine to your blood. When used as directed, Nicotine Polacrilex Lozenges help you regulate, control, and gradually reduce your body's craving for nicotine.

The good news is that Nicotine Polacrilex Lozenges contain no tar or carbon monoxide, and therefore don't present the same medical risks as cigarettes.

However, the lozenges still deliver nicotine, the addictive ingredient in cigarettes. And for some people the nicotine in Nicotine Polacrilex Lozenges can occasionally cause mouth or throat irritation, headaches, nausea, hiccups, upset stomach or dizziness.

USING Nicotine Polacrilex LOZENGES PROPERLY.

Remember, Nicotine Polacrilex Lozenges aren't like ordinary lozenges such as cough drops. This lozenge is designed to deliver nicotine into your system through the lining of your mouth, not in your stomach like most other medicines. It is important to minimize swallowing the dissolved medicine in these lozenges so that it can be properly absorbed in your mouth.

Do not use more than one lozenge at a time, or many lozenges one after another since this can cause hiccups, heartburn, nausea or other side effects.

Read all the following instructions before using Nicotine Polacrilex Lozenges. Refer to them often to make sure you're using Nicotine Polacrilex Lozenges correctly.

IMPORTANT: Don't worry or give up if you do not like the taste of the lozenge at first. Nicotine Polacrilex Lozenges are a medication, not a candy. Most people get used to the taste after a day or two. Remember, staying with the plan will help you quit. Begin using Nicotine Polacrilex Lozenges on your quit date.

1) Remove the Nicotine Polacrilex Lozenge from the immediate container. Place the lozenge in your mouth and allow the lozenge to slowly dissolve (about 20-30 minutes). Minimize swallowing. Do not chew or swallow the lozenge. You may feel a warm or tingling sensation.
2) Occasionally move the lozenge from one side of your mouth to the other side until completely dissolved (about 20-30 minutes).
  To reduce cravings or urges to smoke and other withdrawal symptoms, use Nicotine Polacrilex Lozenges according to the following dosage schedule.

Weeks 1 through 6 | Weeks 7 through 9 | Weeks 10 through 12
1 lozenge every 1 to 2 hours | 1 lozenge every 2 to 4 hours | 1 lozenge every 4 to 8 hours

Do not use more than 5 lozenges in 6 hours. Do not use more than 20 lozenges per day. At the end of 12 weeks (3 months) you will have completed treatment.

FOR THE BEST CHANCE OF QUITTING, use Nicotine Polacrilex Lozenges on a regular schedule, using at least 9 lozenges a day during the first 6 weeks. That will help your body better adjust to the lack of cigarettes and better help prevent cravings. Some people may need more lozenges to reduce their cravings. Do not exceed the recommended maximum daily dosage of 20 lozenges per day. Do not continuously use one lozenge after another, since this may cause you hiccups, heartburn, nausea or other side effects.

Do not eat or drink 15 minutes before using or while the lozenge is in your mouth.

CUTTING BACK ON YOUR Nicotine Polacrilex LOZENGE USAGE.

The whole reason for using Nicotine Polacrilex Lozenges is to decrease and slowly eliminate your need for nicotine, while you control cravings. So, as the above schedule indicates, you should gradually reduce the amount of Nicotine Polacrilex Lozenges you take per day. Some people find it easier to reduce by substituting ordinary sweets or sugar free candy for some of the Nicotine Polacrilex Lozenges they would normally use. As time goes on, you can increase the number of pieces of candy as you further reduce your use of Nicotine Polacrilex Lozenges. It is important to complete treatment. If you still feel the need to use Nicotine Polacrilex Lozenges to keep from smoking after week 12, talk with your health care provider.

MAKE QUITTING EASIER ON YOURSELF.

Soon after your quit date, parties, bars, celebrations, and socializing may all tempt you to smoke. Please remember these tips to help you resist those urges and stay smoke-free.

The Day You Quit Smoking:

- Look to your family and friends for support. Let them know what to do or avoid doing to help you quit.
- Throw away ALL cigarettes, ashtrays, matches, lighters. You don't need them. You don't want them and you want to make it difficult to go back.
- Keep yourself occupied. Take a walk. See a movie. See friends. Do anything to keep your mind off cigarettes.
- Calculate all the money you'll save by not buying cigarettes. Probably well over $1,000 a year! $1,000 a year? Think of what you can spend it on!
- Know what situations are going to make you want to smoke. Plan now how you'll avoid them or deal with them so you don't smoke.
- Keep Nicotine Polacrilex Lozenges next to your bed so you're prepared when you get up. A lot of people get cravings first thing in the morning.
- Make an appointment to see your dentist and get the tobacco stains cleaned off. While you're getting rid of the evidence of cigarettes in the house, do the same for your teeth. Have clothes or drapes that smell of smoking cleaned.
- Now that your house is smoke-free, try to spend most of your time in smoke-free environments.
- If you usually smoked with coffee or alcohol, try to keep away from them for now. Remember you are also trying to break a habit.
- Smoking is a "hands-on" habit. So use something else to occupy your hands: a rubber band or a pen.
- Now's a good time to get active. Find activities to take your mind off cigarettes and relax. Take up jogging, swimming, or walking.
- Don't stress out about gaining weight. Dieting now may weaken your efforts to quit smoking. Eat sensibly and exercise daily; drink large quantities of water and fruit juices; this can help your chances of staying smoke-free.
- Laugh. Watch a sitcom. Read a comic book. It really helps.

REMEMBER: Urges to smoke are temporary. They'll pass, even if you don't smoke.

WHAT YOU CAN EXPECT.

As you are successful at staying smoke-free, initially you will probably notice a few of the following typical withdrawal symptoms, so don't be surprised. Use of Nicotine Polacrilex Lozenges reduces these symptoms, but may not eliminate them entirely. They will go away with time. Stay focused on your goal of becoming an ex-smoker. Research shows that if you manage to avoid all smoking in the first week (that means not having a single puff), your chances of success increase dramatically.

The First Few Days. You may feel nervous or irritable or have difficulty concentrating during the first few days after you quit smoking. Your body needs time to regain balance. Initially, you might feel a little out of sorts, get headaches, feel light-headed, or have trouble sleeping. Your smoker's cough may get worse before it improves. But fear not, it’s a positive sign. Coughing helps clean your lungs of the tar residue you got from smoking.

After a Couple of Weeks. Your confidence and ability to cope with urges to smoke should be getting stronger. But don't be over-confident and think you can smoke just one cigarette. Even now, having even a single puff can lead to a return to smoking cigarettes regularly. Be prepared, and remember why you wanted to stop smoking.

Have you noticed that your sense of taste and smell has improved? You are probably coughing less and finding it easier to breathe. You've also probably noticed your withdrawal symptoms are subsiding (though don't worry if they're still here: they last longer for some people). These are all positive signs that your body is getting used to your success at stopping smoking.

By The End of The First Month. You are less likely to have cravings for cigarettes as often. However sudden cravings may still happen, and when they do, be on your guard, as they can be strong and seem to come out of the blue. Be prepared for these challenging times. The key is do what you can so these unexpected cravings can't beat you. Keep focused on the ways non-smokers are more attractive than smokers. Their breath smells better. Their clothes and hair are fresher. Their teeth are cleaner and brighter. Their skin is less likely to wrinkle. Not smoking around children and your friends is also healthier for them too.

What If You Do Slip And Smoke?

"What if I relapse?" One cigarette is a slip-up, but it's not the end of the quit effort. Everybody slips at something. The key is this: forgive yourself and stop at that one cigarette. Don't let this slip ruin your good intentions, keep at your quit attempt. So, throw out your cigarettes and continue with your quit attempt, keeping in mind what went wrong and led to the slip.

If you do go back to smoking, certainly don't throw out your Nicotine Polacrilex Lozenges. Keep them for the next time you're ready to quit. In fact research says that even if you are back to smoking regularly the best thing you can do is learn and try again.

Try to understand the reason you had those cigarettes that made you slip. That's important, because now you can plan better to deal with these moments next time. It’s true you stumbled, but don't think of yourself as having failed. Encourage yourself by treating the last attempt as a learning experience, even a "trial run" for the real thing.

Take a look at the usage instructions and check that you used the Nicotine Polacrilex Lozenges correctly and for the full 12 weeks of the program. When you try again make sure you use enough and the right way. That way you'll be best equipped to deal with the unexpected cravings.

Don't forget; quitting isn't easy and it takes practice to do anything. Stopping smoking is no different.

YOU'VE MADE IT.

Once your twelve week quitting program is over, you've taken your last Nicotine Polacrilex Lozenge. Now you are both cigarette and nicotine-free. Get up and give yourself a standing ovation. We mean it. Do you realize that you have just done a really difficult thing?

Now's a good time to think back on the process. Think of all your reasons for quitting smoking. Think of your goals. Think of how they're going to be a reality now.

Think of what you're going to do with your newly liberated cigarette money. The places you can now go smoke-free. Think of the extra time you may have added to your life and what you can do with it. And although you may still experience the occasional temptation, and cigarettes still want you back, think positively. Think forward. And consider yourself a proud non-smoker.

FREQUENTLY ASKED QUESTIONS.

1. When I stop smoking and start using Nicotine Polacrilex Lozenges how will I feel?

Nicotine Polacrilex Lozenges help reduce cravings, but be prepared for some nicotine withdrawal symptoms. After you stop smoking they can begin almost at once and are normally at their strongest during the first three or four days. For some people, any of the following may occur:

- unexpected craving or urges for cigarettes
- anxiety, irritability, restlessness, mood changes, nervousness
- drowsiness
- trouble concentrating
- increased appetite and weight gain
- headaches, muscular pain, constipation, fatigue

Nicotine Polacrilex Lozenges are designed to reduce the craving for nicotine you used to satisfy with cigarettes. Nicotine Polacrilex Lozenges can also help provide relief from other withdrawal symptoms such as irritability and nervousness.

2. Are Nicotine Polacrilex Lozenges just swapping one type of nicotine addiction for another?

Nicotine Polacrilex Lozenges do contain nicotine, however there is probably less nicotine in your daily dose of lozenges than in your cigarettes. Nicotine Polacrilex Lozenges give you enough nicotine to help you combat the physical withdrawal symptoms so you can cope with the mental side of stopping smoking. Also, since the nicotine from the lozenges goes into your bloodstream more slowly, it produces less of the effects of nicotine that people find rewarding. In fact, when used as directed in the 12 week program, Nicotine Polacrilex Lozenges gradually wean you off your dependence for both nicotine and cigarettes.

3. Can Nicotine Polacrilex Lozenges do any harm?

Some people with conditions like heart disease or people taking prescription medicine for asthma or depression should not use this product without talking to their doctor - check the IMPORTANT WARNINGS on the front of this leaflet. You may also experience side effects such as hiccups, mouth or throat irritation, heartburn or other stomach problems such as nausea especially if Nicotine Polacrilex Lozenges are chewed or swallowed. In any case, Nicotine Polacrilex Lozenges do not contain the tar, carbon monoxide, and other toxins present in cigarette smoke.

4. Will I put on weight?

In the first couple of months after quitting smoking, some people do put on a few pounds. But think of it this way. Overall, you'll be healthier and look better. You can always tackle your weight by changing your diet and increasing the amount you exercise once you have gotten through the difficult part of stopping smoking.

5. Does taking Nicotine Polacrilex Lozenges cost more than smoking?

If you normally smoke a pack and a half a day, your total cost of using Nicotine Polacrilex Lozenges during the 12-week period should be less than smoking. But guess what? After you've finished the Nicotine Polacrilex Lozenge program all that money you used to spend on cigarettes is now savings. And think of the health issues you'll hopefully be able to avoid.

6. What if I have a cigarette and start smoking?

Don't panic. First, don't think badly of yourself. Throw away your cigarettes and forgive yourself. Then think about what went wrong and get back on track. In fact people who have already tried to stop smoking are more likely to be successful the next time.

CHALLENGES TO WATCH FOR.

Once you quit smoking, you are likely to experience periodic, and sometimes intense, temptations to smoke. Certain situations present special challenges. Some common ones include:

Stress and upset.

When you are feeling stressed or upset, you may think a cigarette will make everything better. It won’t. Find other ways to relax and unwind.

The blues.

You may be especially vulnerable when you feel bored or blue. Remember that having a cigarette will just make you feel worse.

Smoking cues.

Seeing cigarettes or watching other people smoke can trigger temptation. Remember that you choose not to smoke anymore.

Alcohol.

Drinking and smoking seem to go together, and alcoholic beverages may weaken your resolve, making drinking dangerous to your quit effort. Avoid drinking early in your quit effort, and try to drink with non-smokers.

Automatic slips.

Sometimes you may find yourself preparing to smoke without even realizing it. Watch out for those moments when your hand seems to 'automatically' reach for a cigarette.

Watch out for these situations: they can trigger a relapse. You probably know which one(s) are most dangerous for you; plan ahead to deal with the situation effectively. Always remember that you're trying to break a habit, and the most important thing is to do something to combat the urge in these situations.

COPING AFTER QUITTING.

The key to staying smoke-free is to prepare for and cope with challenges as they occur. If you find yourself tempted to smoke, do something! Here are some things to consider.

- Escape. Leave the situation, even for a few minutes. Most temptations don't last long.
- Distract yourself. Get your mind off smoking. Think of something else or get busy with something.
- Relax. Don't let stress get to you. Think of pleasant, relaxing things; breathe slowly and regularly. Let the stress drain out of you.
- Talk yourself out of it. What you say to yourself matters. So, remind yourself how important it is for you to quit; remind yourself you can't have just one; or just command yourself to STOP.

For more information please visit www.SmokeFreeHabits.com

Free Personalized Plan

Begin Right Now!

Having a plan will help you in your efforts to stop smoking. We can help! Follow the simple steps below to receive your valuable personalized Smoke Free Habits plan and many other stop smoking tools and resources.

How To Enroll

Stopping smoking involves breaking your physical addiction and changing your behavior. You will use Nicotine Polacrilex Lozenges to help break your physical addiction, while your free personalized plan will help you develop healthier behaviors.

To enroll:

- Go online to www.SmokeFreeHabits.com
- Enter the first five digits of the UPC number from the box.
- Answer the questions about yourself.
- Print your personalized plan.

(If you don't have access to the Internet, you can call 1-866-751-9303, answer questions, and your plan will be mailed to you in a few days.)

What You Will Receive

Here are the free tools and resources that you will receive based on how you sign up for the program:

 | Online | By Phone
Personalized 12-Week Plan | immediately | by mail
Buddy Brochure | immediately | by mail
Personal Wellness Assessment | immediately
Week 2 Helpful Tips | X
Week 3 Helpful Tips | X | by mail
Week 4 Helpful Tips | X
Week 6 Helpful Tips | X | by mail
Week 9 Helpful Tips | X
Week 12 Certificate of Accomplishment | X | by mail
Online Drug Database | X
Daily Health News | X

Tips To Get Started

1. Follow your personalized Smoke Free Habits support plan.
2. Be sure to use Nicotine Polacrilex Lozenges as directed.
3. Throw away all of your cigarettes, lighters, and ashtrays.
4. You may feel urges to smoke, but they usually pass in 2-3 minutes. When you feel an urge, do something else. Take deep breaths and let them out slowly. Drink a glass of water.
5. Carry things to put in your mouth, like gum, hard candy or toothpicks.
6. Be active. Take a walk with a friend, ride your bike, walk the dog, play tennis.
7. Go to places where you are not allowed to smoke, like the movies or the mall. Try to steer clear of places where you usually smoked, like a break room at work or a favorite bar.
8. Ask friends or family for support whenever you need it.

Packaged By

Perrigo®

Allegan, MI 49010

: 87300 00 J2

Principal Display Panel

Walgreens

WALGREENS PHARMACIST RECOMMENDED

Compare to the active ingredient in Nicorette® Lozenge

Nicotine Lozenge

NICOTINE POLACRILEX LOZENGE 4 mg (NICOTINE)

STOP SMOKING AID

Sugar Free

• Includes user’s guide

108 LOZENGES

4 mg

ACTUAL SIZE

Cherry flavor

(4 QuitTube® CONTAINERS OF 27)

4 mg EACH

FOR THOSE WHO SMOKE THEIR FIRST CIGARETTE WITHIN 30 MINUTES OF WAKING UP.

If you smoke your first cigarette MORE THAN 30 MINUTES after waking up, use Nicotine Polacrilex Lozenge, 2 mg.